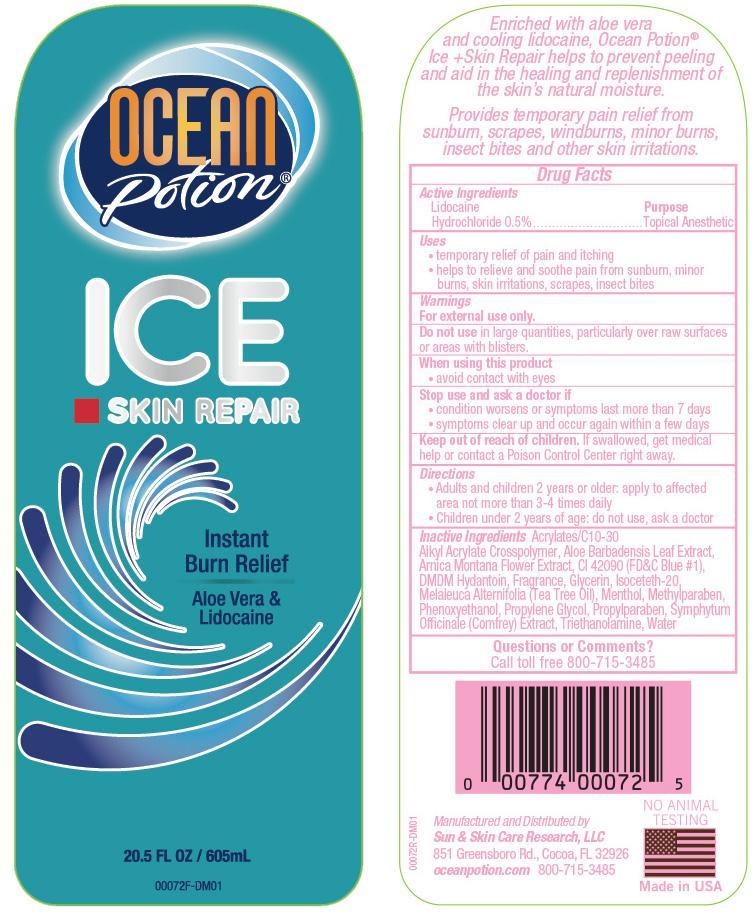 DRUG LABEL: Ocean Potion Instant Burn Relief Ice
NDC: 62802-172 | Form: GEL
Manufacturer: Sun & Skin Care Research, LLC
Category: otc | Type: HUMAN OTC DRUG LABEL
Date: 20140321

ACTIVE INGREDIENTS: LIDOCAINE .5 g/100 g
INACTIVE INGREDIENTS: WATER; ISOCETETH-20; PROPYLENE GLYCOL; ALOE VERA LEAF; GLYCERIN; MENTHOL; CARBOMER COPOLYMER TYPE A (ALLYL PENTAERYTHRITOL CROSSLINKED); DMDM HYDANTOIN; PHENOXYETHANOL; METHYLPARABEN; PROPYLPARABEN; TROLAMINE; ARNICA MONTANA FLOWER; COMFREY LEAF; TEA TREE OIL; FD&C BLUE NO. 1

DRUG FACTS

Active Ingredient

Lidocaine 0.5%

Purpose

Temporarily Relieves pain due to:

- sunburn
- minor burns

Uses

Temporarily Relieves pain and itching due to:

- sunburn
- minor burns

Warnings

For external use only. Do not swallow. Avoid contact with eyes. If contacted, flush eyes with water. Should a rash or irritation develops, discontinue use. If condition worsens, or if symptoms persist for more than 7 days, consult a physician. Do not use in large quantities, particularly over raw surfaces or blistered areas. Keep out of the reach of children.

Keep out of reach of children. If swallowed, get medical help or contact a Poison Control Center right away.

INACTIVE INGREDIENT SECTION

Inactive Ingredients: Acrylates / C10-30 Alkyl Acrylate Crosspolymer, Aloe Barbadensis Leaf Extract, Arnica Montana Flower Extract, CI 42090, DMDM Hydantoin, Fragrance, Glycerin, Isoceteth-20, Melaleuca Alternifolia (Tea Tree Oil), Menthol, Methylparaben, Phenoxyethanol, Propylene Glycol, Propylparaben, Symphytum Officinale (Comfrey) Extract, Triethanolamine, Water

Directions

Adults and children 2 years of age and older, apply to the affected area not more than 3 to 4 times daily. Children under 2 years of age, consult a physician.

STORAGE AND HANDLING

- protect this product from excessive heat and direct sun
- for use on skin only